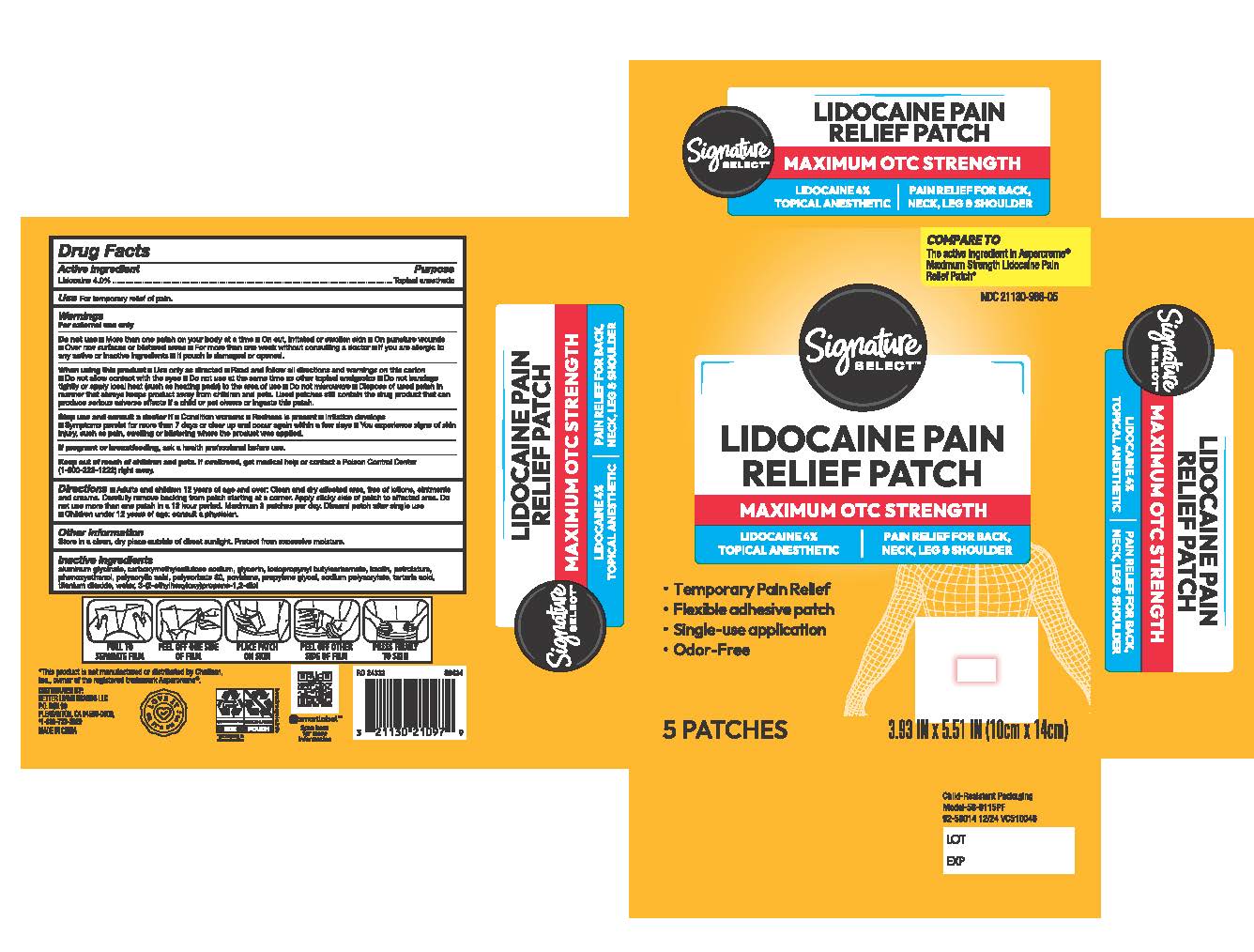 DRUG LABEL: Signature Care Medicated Pain Relief  Patch
NDC: 21130-988 | Form: PATCH
Manufacturer: Safeway, Inc.
Category: otc | Type: HUMAN OTC DRUG LABEL
Date: 20250212

ACTIVE INGREDIENTS: LIDOCAINE 4 g/100 g
INACTIVE INGREDIENTS: GLYCERIN; KAOLIN; POLYETHYLENE GLYCOL 400; POVIDONE; ETHYLHEXYLGLYCERIN; CARBOXYMETHYLCELLULOSE SODIUM; PHENOXYETHANOL; PETROLATUM; DIHYDROXYALUMINUM AMINOACETATE; TITANIUM DIOXIDE; WATER; SODIUM POLYACRYLATE (8000 MW); TARTARIC ACID; IODOPROPYNYL BUTYLCARBAMATE; POLYACRYLIC ACID (8000 MW); POLYSORBATE 80

Signature Care Medicated Pain Relief Patch

Active Ingredient

Lidocaine

Purpose

Topical anesthetic

Use

For temporary relief of pain

Warning

For external use

Do not use

■ More than one patch on your body at a time ■On cut, irritated or swollen skin ■On puncture wounds ■Over raw surfaces or blistered areas ■ For more than one week without consulting a doctor ■ If you are allergic to any active or inactive ingredients■ If pouch is damaged or opened.

When using this product

■Use only as directed■Read and follow all directions and warnings on this carton ■Do not allow contact with the eyes ■Do not use at the same time as other topical analgesics ■Do not bandage tightly or apply local heat (such as heating pads) to the area of use ■ Do not microwave ■Dispose of used patch in manner that always keeps product away from children and pets.
Used patches still contain the drug product that can produce serious adverse effects if a chIld or pet chews or ingests this patch.

Stop use and consult a doctor if

■ Condition worsens ■ Redness is present ■ Irritation develops ■ Symptoms persist for more than 7 days or clear up and occur again within a few days■ You experience signs of skin injury, such as pain, swelling or blistering where the product was applied.

If pregnant or breastfeeding

ask a health professional before use.

Keep out of reach of children and pets.

If swallowed, get medical help or contact a Poison Control Center (1-800-222-1222) right away.

Directions

■Adults and children 12 years of age and over: Clean and dry affected area, free of lotions, ointments and creams. Carefully remove backing from patch starting at a corner. Apply sticky side of patch to affected area. Do not use more than one patch in a 12 hour period. Maximum 2 patches per day. Discard patch after single use ■Children under 12 years of age: consult a physician.

Other information

Store in a clean, dry place outside of direct sunlight. Protect from excessive moisture.

Inactive ingredients

aluminum glycinate, carboxymethylcellulose sodium, glycerin, iodopropynyl butylcarbamate, kaolin, petrolatum, phenoxyethanol, polyacrylic acid, polysorbate 80, povidone, propylene glycol, sodium polyacrylate, tartaric acid, titanium dioxide, water, 3-(2-ethylhexyloxy)propane-1,2-diol